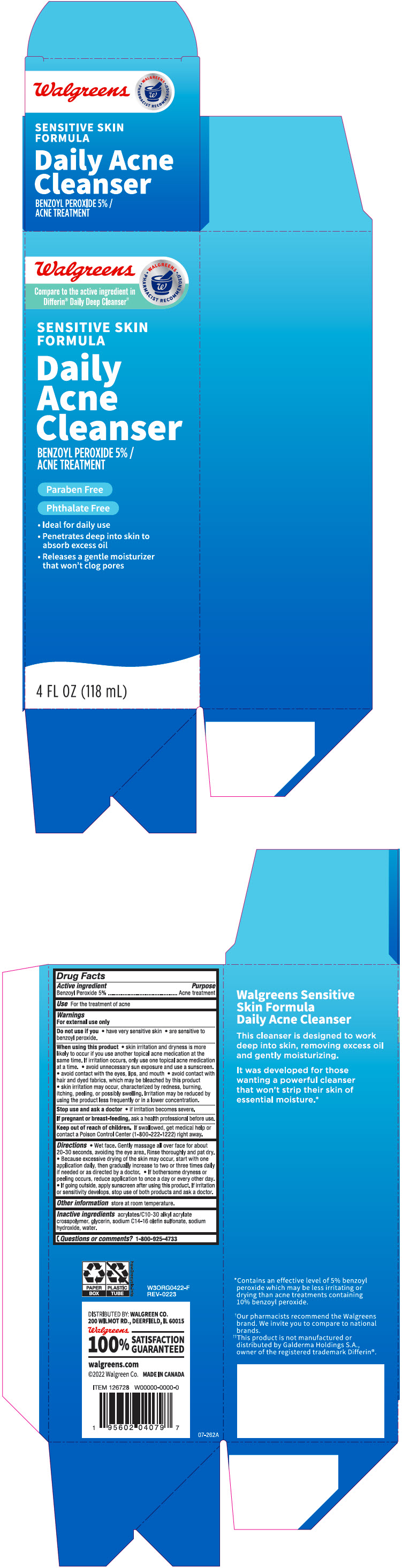 DRUG LABEL: Walgreens Daily Acne Cleanser- Sensitive Skin Formula
NDC: 0363-5602 | Form: LOTION
Manufacturer: Walgreen Company
Category: otc | Type: HUMAN OTC DRUG LABEL
Date: 20240501

ACTIVE INGREDIENTS: Benzoyl Peroxide 50 mg/1 mL
INACTIVE INGREDIENTS: Glycerin; Sodium C14-16 Olefin Sulfonate; Sodium Hydroxide; Water

Walgreens Daily Acne Cleanser- Sensitive Skin Formula
Acne Treatment

Drug Facts

Active ingredient

Benzoyl Peroxide 5%

Purpose

Acne treatment

Use

for treatment of acne

Warnings

For external use only.

Do not use if you

- have very sensitive
- are sensitive to benzoyl peroxide

When using this product

- skin irritation and dryness are more likely to occur if you use another topical acne medication at the same time. If irritation occurs, only use one topical acne medication at a time
- avoid unnecessary sun exposure and use a sunscreen
- avoid contact with the eyes, lips and mouth
- avoid contact with hair and dyed fabrics, which may be bleached by this product
- skin irritation may occur, characterized by redness, burning, itching, peeling, or possibly swelling. Irritation may be reduced by using the product less frequently or in a lower concentration.

Stop use and ask a doctor if

- irritation becomes severe.

PREGNANCY OR BREAST FEEDING

If pregnant or breast-feeding, ask a health professional before use.

Keep out of reach of children. If swallowed, get medical help or contact a Poison Control Center (1-800-222-1222) right away.

Directions

- Wet face. Gently massage all over face for about 20-30 seconds, avoiding the eye area. Rinse thoroughly and pat dry.
- Because excessive drying of the skin may occur, start with one application daily, then gradually increase to two to three times daily if needed or as directed by a doctor
- if bothersome dryness or peeling occurs, reduce application to once a day or every other day
- if going outside, apply sunscreen after using this product. If irritation or sensitivity develops, stop use of both products and ask a doctor.

Other information

Store at room temperature

Inactive ingredients

acrylates/C10-30 alkyl acrylate crosspolymer, glycerin, sodium C14-16 olefin sulfonate, sodium hydroxide, water.

Questions or comments?

1-800-925-4733

DISTRIBUTED BY: WALGREEN CO.
200 WILMOT RD., DEERFIELD, IL 60015

PRINCIPAL DISPLAY PANEL - 118 mL Tube Carton

Walgreens

Compare to the active ingredient in
Differin® Daily Deep Cleanser††

• WALGREENS •
PHARMACIST RECOMMENDED†

SENSITIVE SKIN
FORMULA

Daily
Acne
Cleanser

BENZOYL PEROXIDE 5% /
ACNE TREATMENT

Paraben Free
Phthalate Free

- Ideal for daily use
- Penetrates deep into skin to
  absorb excess oil
- Releases a gentle moisturizer
  that won't clog pores

4 FL OZ (118 mL)